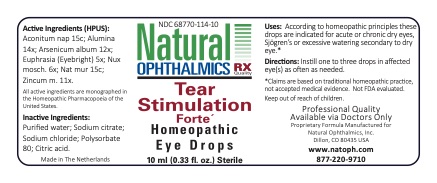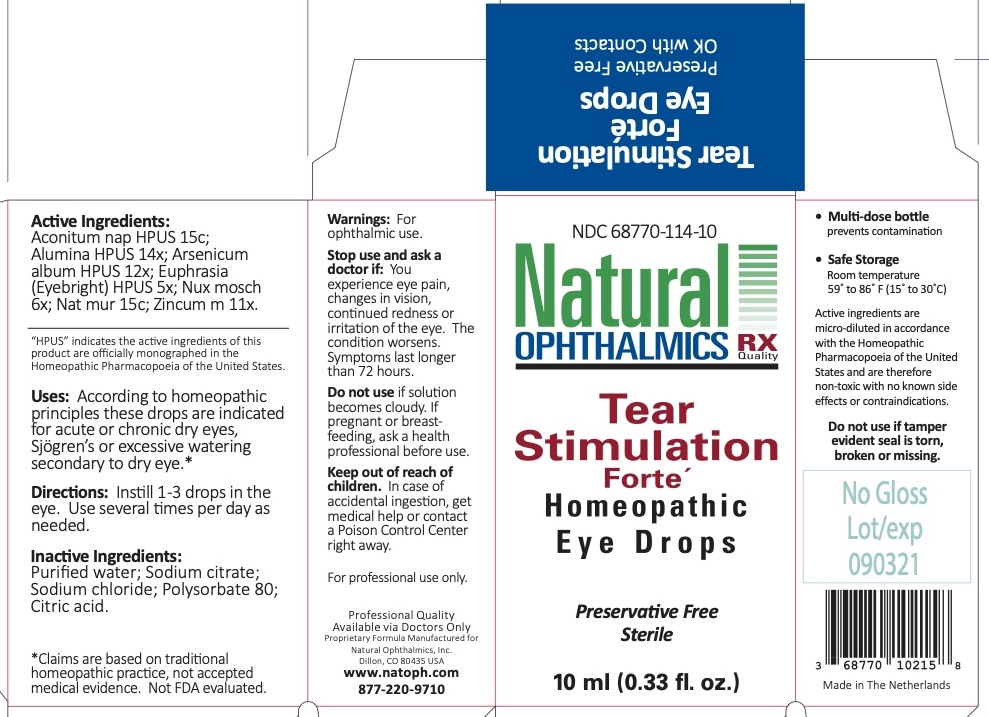 DRUG LABEL: Tear Stimulation Forte
NDC: 68770-114 | Form: LIQUID
Manufacturer: Natural Ophthalmics, Inc
Category: homeopathic | Type: HUMAN OTC DRUG LABEL
Date: 20220707

ACTIVE INGREDIENTS: SODIUM CHLORIDE 15 [hp_C]/1 mL; ACONITUM NAPELLUS 15 [hp_C]/1 mL; EUPHRASIA STRICTA 5 [hp_X]/1 mL; ALUMINUM OXIDE 14 [hp_X]/1 mL; ARSENIC TRIOXIDE 12 [hp_X]/1 mL; NUTMEG 6 [hp_X]/1 mL; ZINC 11 [hp_X]/1 mL
INACTIVE INGREDIENTS: WATER; POLYSORBATE 80; CITRIC ACID MONOHYDRATE

Tear Stimulation Forte

Active Ingredients

Aconitum nap HPUS 15c
Alumina HPUS 14x
Arsenicum album HPUS 12x
Euphrasia (Eyebright) HPUS 5x
Nux mosch 6x
Nat mur 15c
Zincum met 11x

Uses

According to homeopathic principles these drops are indicated for acute or chronic dry eyes, Sjögren’s or excessive watering secondary to dry eye.*

* Claims are based on traditonal homeopathic practce, not accepted medical evidence. Not FDA evaluated.

Directions

Instill 1-3 drops in the eye. Use several times per day as needed.

Homeopathic Purpose

- Pulsatilla 8x }
- Sepia 8x }
- Euphrasia (Eyebright) 5x }
  - Alumina 10x } Dry eyes
- Arsenicum album 12x }
- Nux mosch 6x }
- Zincum met 10x }

Inactive Ingredients

Purified water
Sodium citrate

Sodium chloride

Polysorbate 80

Citric acid

Warnings

For ophthalmic use.

Stop use and ask a doctor if: You experience eye pain, changes in vision, continued redness or irritation of the eye. The condition worsens. Symptoms last longer than 72 hours.

Do not use if solution becomes cloudy.

If pregnant or breast feeding, ask a health professional before use.

Keep out of reach of children. In case of accidental ingestion, get medical help or contact a Poison Control Center right away.

Storage

- Safe Storage

Room temperature
59o to 86o (15o to 30o C)